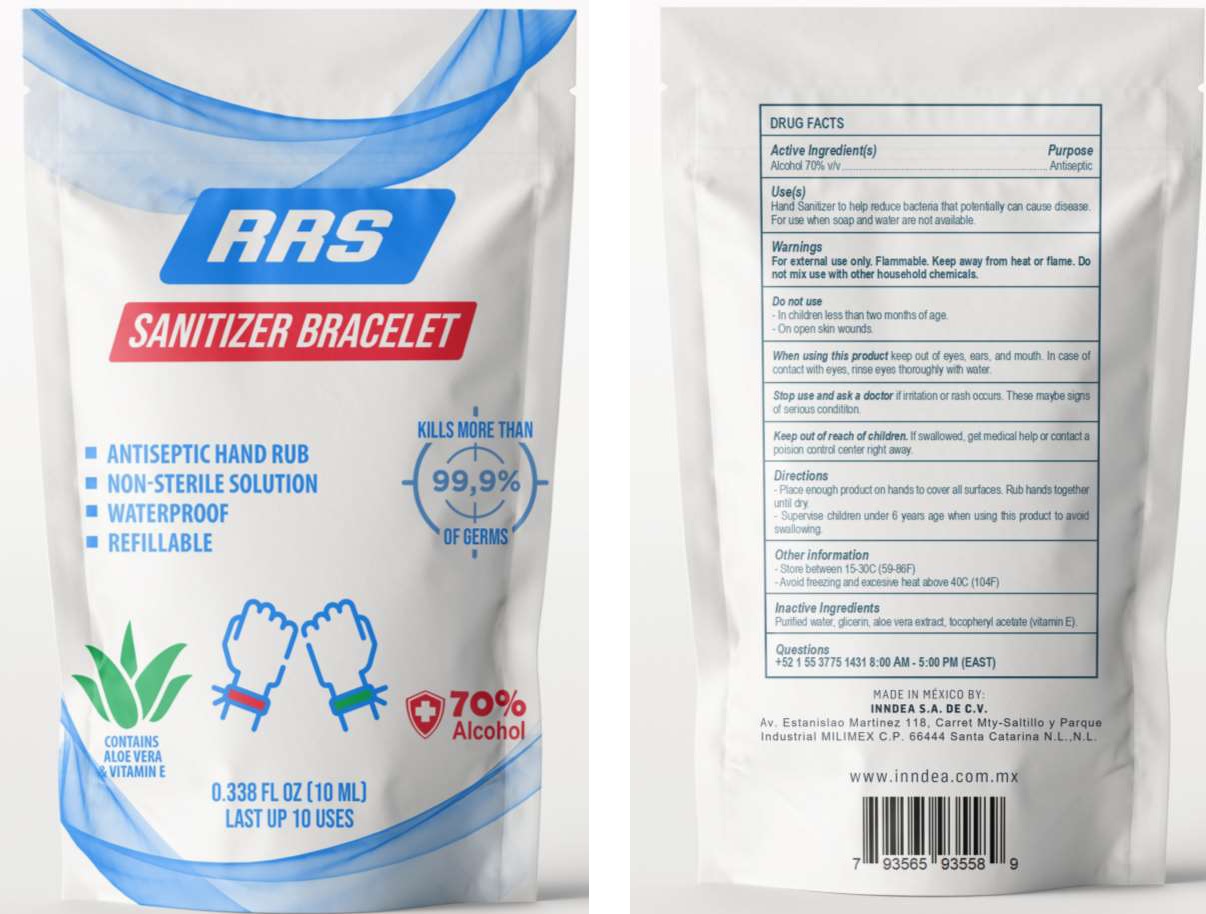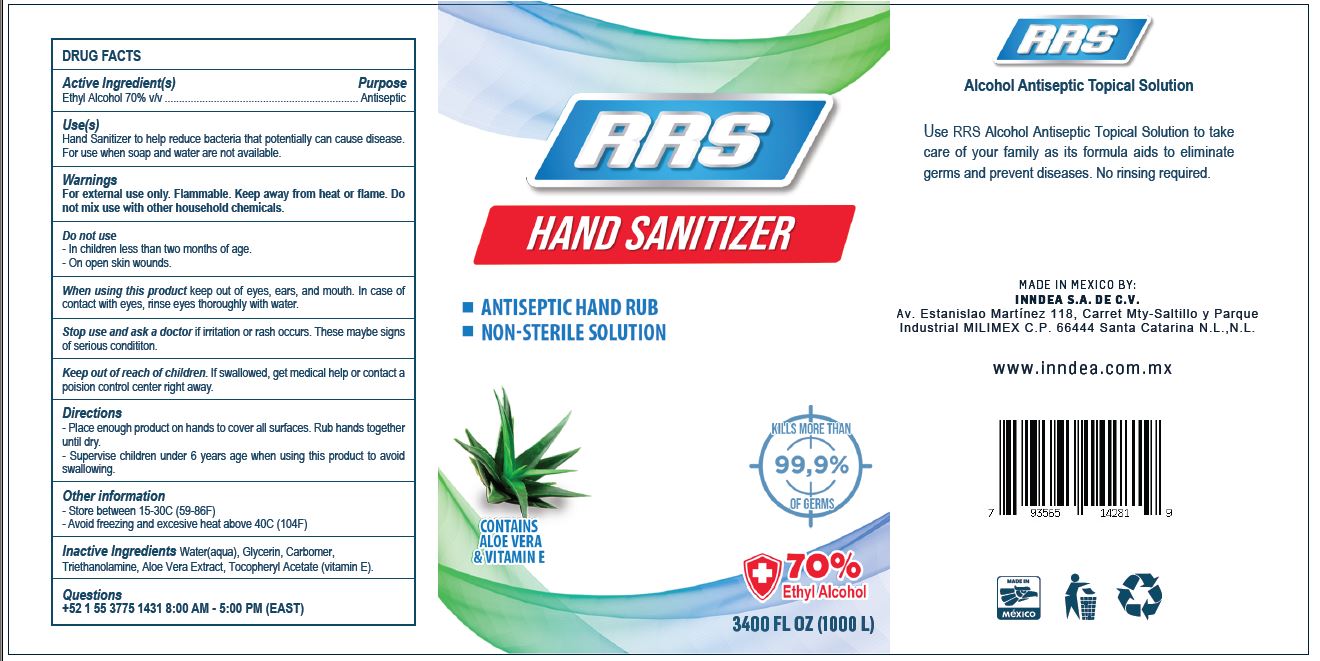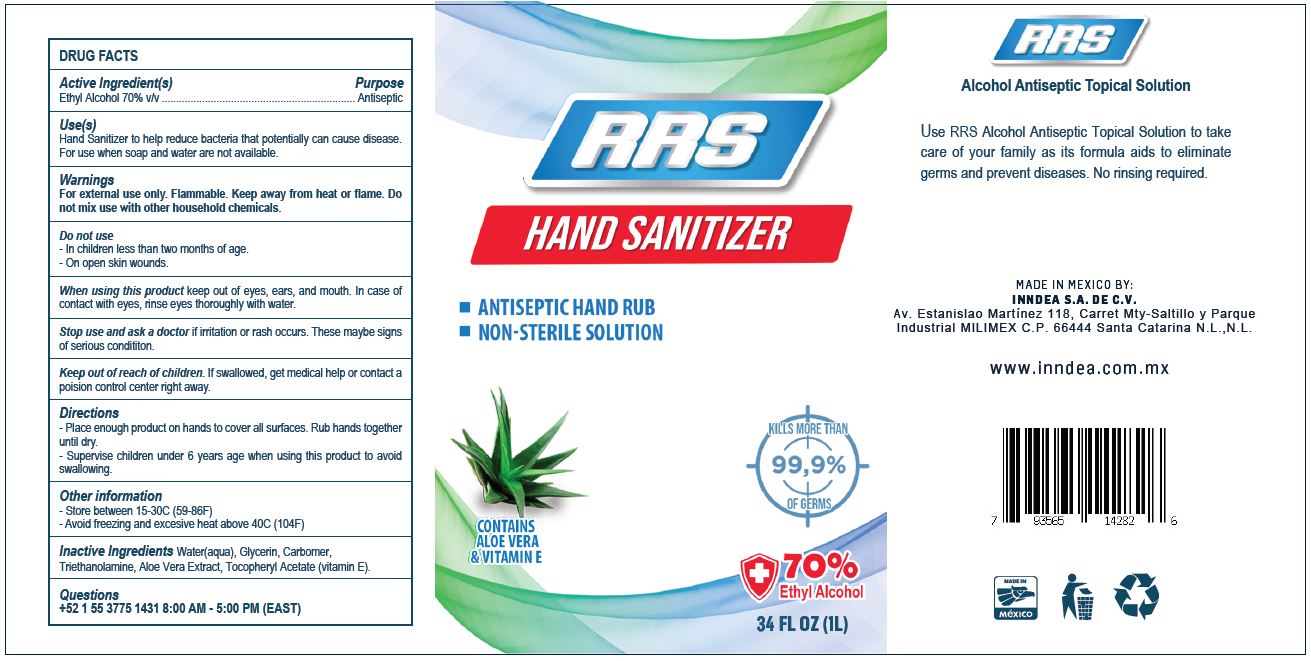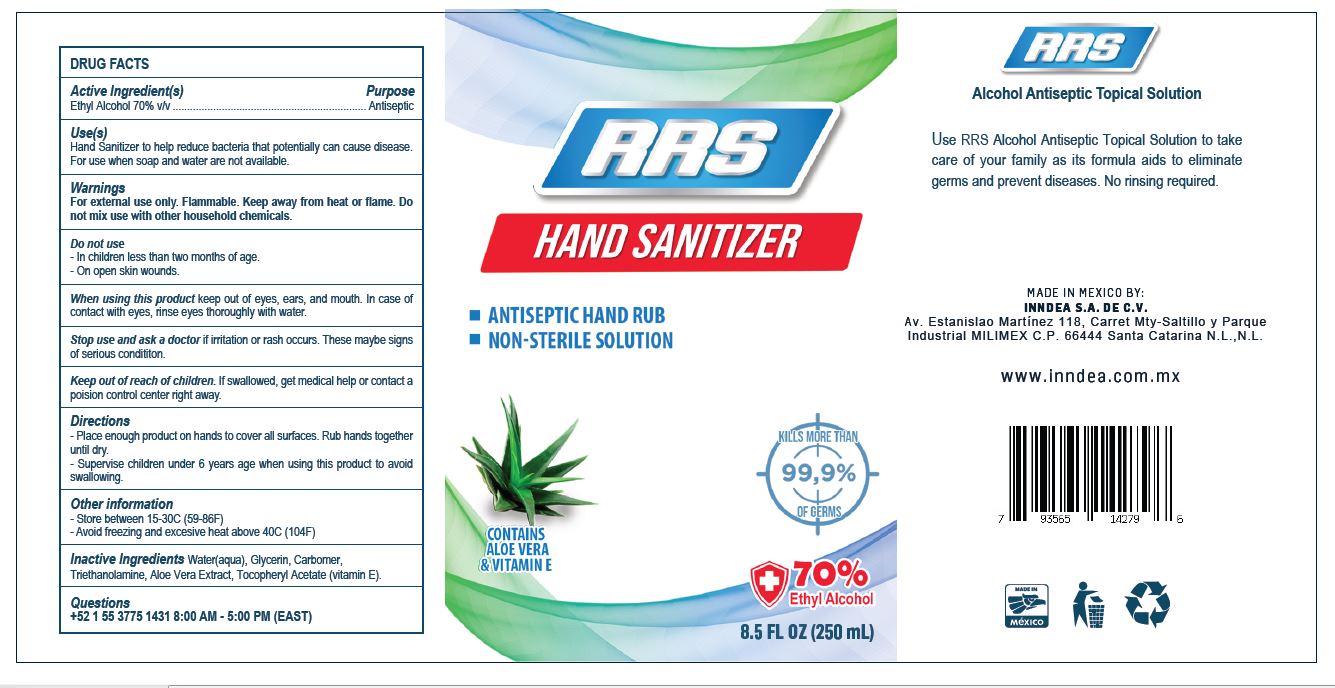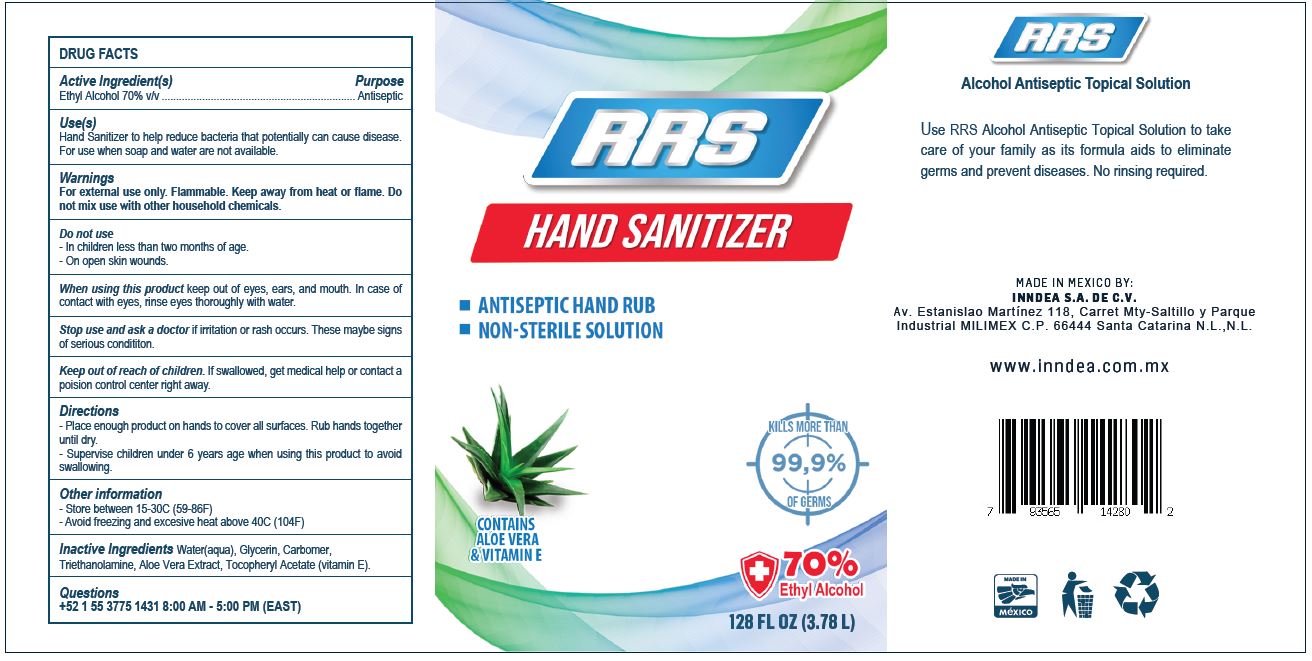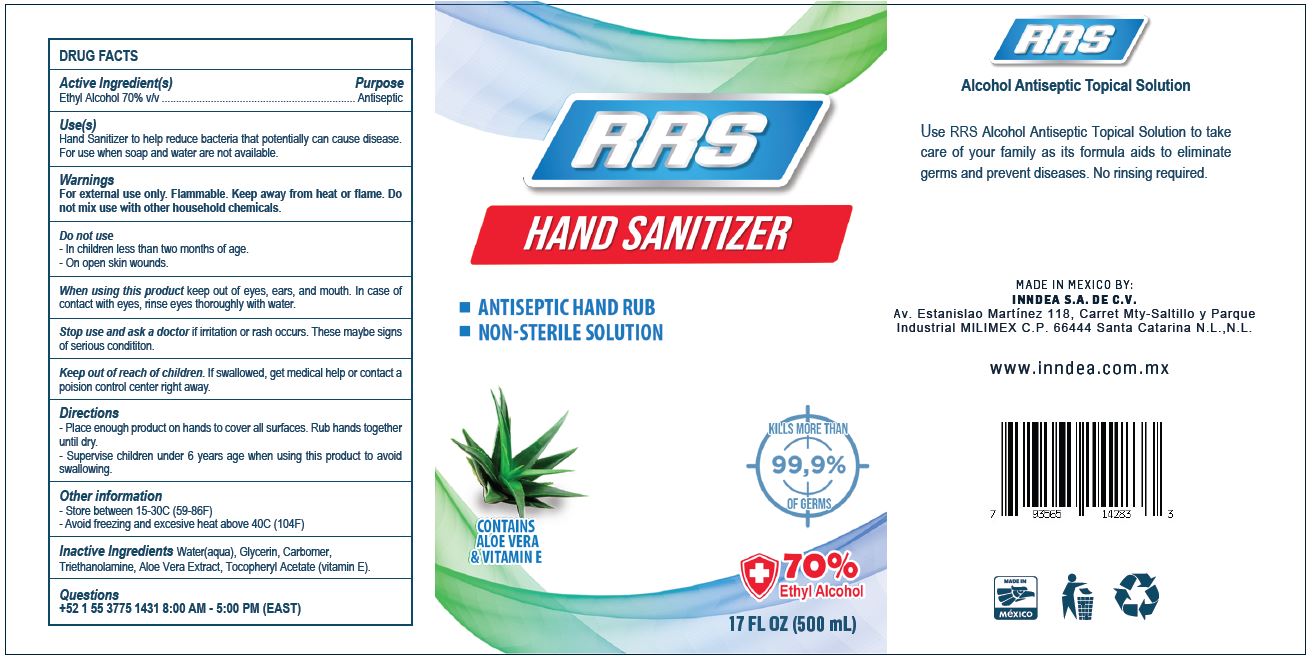 DRUG LABEL: Hand Sanitizer
NDC: 79875-000 | Form: GEL
Manufacturer: INNDEA, S.A. de C.V.
Category: otc | Type: HUMAN OTC DRUG LABEL
Date: 20200805

ACTIVE INGREDIENTS: ALCOHOL 0.7 mL/1 mL
INACTIVE INGREDIENTS: WATER; GLYCERIN; ALOE VERA LEAF; .ALPHA.-TOCOPHEROL ACETATE

Hand Sanitizer

Active Ingredient(s)

Ethyl Alcohol 70% v/v

Purpose

Antiseptic

Use(s)

Hand Sanitizer to help reduce bacteria that potentially can cause disease. For use when soap and water are not available.

Warnings

For external use only. Flammable. Keep away from heat or flame. Do not mix use with other household chemicals.

Do not use

- In children less than two months of age.
- On open skin wounds.

When using this product

keep out of eyes, ears, and mouth. In case of contact with eyes, rinse eyes thoroughly with water.

Stop use and ask a doctor

if irritation or rash occurs. These maybe signs of serious condititon.

Keep out of reach of children.

If swallowed, get medical help or contact a poision control center right away.

Directions

- Place enough product on hands to cover all surfaces. Rub hands together until dry.
- Supervise children under 6 years age when using this product to avoid swallowing.

Other information

- Store between 15-30C (59-86F)
- Avoid freezing and excesive heat above 40C (104F)

Inactive Ingredients

Purified water, glicerin, aloe vera extract, tocopheryl acetate (vitamin E).

Questions

+52 1 55 3775 1431 8:00 AM - 5:00 PM (EAST)